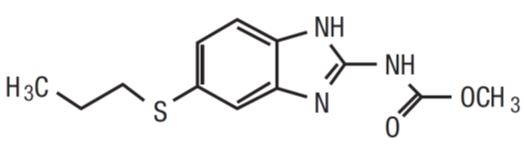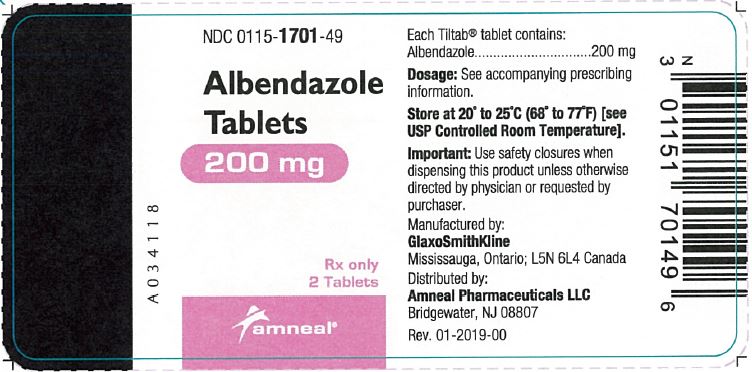 DRUG LABEL: Albendazole
NDC: 0115-1701 | Form: TABLET, FILM COATED
Manufacturer: Amneal Pharmaceuticals of New York LLC
Category: prescription | Type: HUMAN PRESCRIPTION DRUG LABEL
Date: 20190930

ACTIVE INGREDIENTS: ALBENDAZOLE 200 mg/1 1
INACTIVE INGREDIENTS: CARNAUBA WAX; HYPROMELLOSES; LACTOSE MONOHYDRATE; MAGNESIUM STEARATE; CELLULOSE, MICROCRYSTALLINE; POVIDONE; SODIUM LAURYL SULFATE; SACCHARIN SODIUM MONOHYDRATE; SODIUM STARCH GLYCOLATE TYPE A POTATO; STARCH, CORN

HIGHLIGHTS OF PRESCRIBING INFORMATION

These highlights do not include all the information needed to use ALBENDAZOLE TABLETS safely and effectively. See full prescribing information for ALBENDAZOLE TABLETS.
ALBENDAZOLE tablets, for oral use
Initial U.S. Approval: 1996

1 INDICATIONS AND USAGE

Albendazole is an anthelmintic drug indicated for:

- Treatment of parenchymal neurocysticercosis due to active lesions caused by larval forms of the pork tapeworm, Taenia solium. (1.1)
- Treatment of cystic hydatid disease of the liver, lung, and peritoneum, caused by the larval form of the dog tapeworm, Echinococcus granulosus. (1.2)

2 DOSAGE AND ADMINISTRATION

Patients weighing 60 kg or greater, 400 mg twice daily; less than 60 kg, 15 mg/kg/day in divided doses twice daily (maximum total daily dose 800 mg). Albendazole tablets should be taken with food. (2)

- Hydatid disease: 28-day cycle followed by 14-day albendazole-free interval for a total of 3 cycles. (2)
- Neurocysticercosis: 8 to 30 days. (2)

See additional important information in the Full Prescribing Information. (2)

3 DOSAGE FORMS AND STRENGTHS

- Tablet: 200 mg (3)

4 CONTRAINDICATIONS

Patients with known hypersensitivity to the benzimidazole class of compounds or any components of albendazole.

5 WARNINGS AND PRECAUTIONS

- Bone Marrow Suppression: Fatalities have been reported due to bone marrow suppression; monitor blood counts in all patients at the beginning of each 28-day cycle of therapy, and every 2 weeks while on therapy. Discontinue albendazole if clinically significant changes in blood counts occur. (5.1, 5.4)
- Embryo-fetal Toxicity: Obtain pregnancy test in women of reproductive potential prior to therapy and avoid usage in pregnant women except in clinical circumstances where no alternative management is appropriate. Discontinue therapy if pregnancy occurs and apprise patient of potential hazard to the fetus. (5.2)
- Risk of Neurologic Symptoms: Neurocysticercosis patients may experience cerebral hypertensive episodes, seizures or focal neurologic deficits after initiation of therapy; begin appropriate steroid and anticonvulsant therapy. (5.3)
- Risk of Retinal Damage in Retinal Cysticercosis: Cases of retinal involvement have been reported; examine the patient for the presence of retinal lesions before initiating therapy for neurocysticercosis. (5.4)
- Hepatic Effects. Elevations of liver enzymes may occur. Monitor liver enzymes before the start of each treatment cycle and at least every 2 weeks while on albendazole therapy and discontinue if clinically significant elevations occur. (5.5)

6 ADVERSE REACTIONS

- Adverse reactions 1% or greater in hydatid disease: abnormal liver function tests, abdominal pain, nausea/vomiting, reversible alopecia, headache, dizziness/vertigo, fever. (6.1)
- Adverse reactions 1% or greater in neurocysticercosis: headache, nausea/vomiting, raised intracranial pressure, meningeal signs. (6.1)

To report SUSPECTED ADVERSE REACTIONS, contact Amneal Pharmaceuticals at 1-877-835-5472 or FDA at 1-800-FDA-1088 or www.fda.gov/medwatch.

7 DRUG INTERACTIONS

- Dexamethasone: Steady-state trough concentrations of albendazole sulfoxide were about 56% higher when dexamethasone was coadministered with each dose of albendazole. (7.1)
- Praziquantel: In the fed state increased mean maximum plasma concentration and area under the curve of albendazole sulfoxide by about 50% in healthy subjects. (7.2)
- Cimetidine: Increased albendazole sulfoxide concentrations in bile and cystic fluid by about 2-fold in hydatid cyst patients. (7.3)
- Theophylline: Albendazole induces cytochrome P450 1A in human hepatoma cells; therefore, it is recommended that plasma concentrations of theophylline be monitored during and after treatment. (5.5, 7.4)

FULL PRESCRIBING INFORMATION

1 INDICATIONS AND USAGE

1.1 Neurocysticercosis

Albendazole is indicated for the treatment of parenchymal neurocysticercosis due to active lesions caused by larval forms of the pork tapeworm, Taenia solium.

1.2 Hydatid Disease

Albendazole is indicated for the treatment of cystic hydatid disease of the liver, lung, and peritoneum, caused by the larval form of the dog tapeworm, Echinococcus granulosus.

2 DOSAGE AND ADMINISTRATION

2.1 Dosage

Dosing of albendazole will vary depending upon the indication. Albendazole tablets may be crushed or chewed and swallowed with a drink of water. Albendazole tablets should be taken with food [see Clinical Pharmacology (12.3)].

Table 1: Albendazole Dosage

Indication | Patient Weight | Dose | Duration
Hydatid Disease | 60 kg or greater | 400 mg twice daily, with meals | 28-day cycle followed by a 14-day albendazole-free interval, for a total of 3 cycles
Hydatid Disease | Less than 60 kg | 15 mg/kg/day given in divided doses twice daily with meals (maximum total daily dose 800 mg) | 28-day cycle followed by a 14-day albendazole-free interval, for a total of 3 cycles
Neurocysticercosis | 60 kg or greater | 400 mg twice daily, with meals | 8 to 30 days
Neurocysticercosis | Less than 60 kg | 15 mg/kg/day given in divided doses twice daily with meals (maximum total daily dose 800 mg) | 8 to 30 days

2.2 Concomitant Medication to Avoid Adverse Reactions

Patients being treated for neurocysticercosis should receive appropriate steroid and anticonvulsant therapy as required. Oral or intravenous corticosteroids should be considered to prevent cerebral hypertensive episodes during the first week of treatment [see Warnings and Precautions (5.3)].

2.3 Monitoring for Safety Before and During Treatment

- Monitor blood counts at the beginning of each 28-day cycle of therapy, and every 2 weeks while on therapy with albendazole in all patients [see Warnings and Precautions (5.1)].
- Monitor liver enzymes (transaminases) at the beginning of each 28-day cycle of therapy, and at least every 2 weeks during treatment with albendazole in all patients [see Warnings and Precautions (5.5)].
- Obtain a pregnancy test in women of reproductive potential prior to therapy [see Warnings and Precautions (5.2)].

3 DOSAGE FORMS AND STRENGTHS

- Tablet: 200 mg

4 CONTRAINDICATIONS

Albendazole is contraindicated in patients with known hypersensitivity to the benzimidazole class of compounds or any components of albendazole.

5 WARNINGS AND PRECAUTIONS

5.1 Bone Marrow Suppression

Fatalities associated with the use of albendazole have been reported due to granulocytopenia or pancytopenia. Albendazole may cause bone marrow suppression, aplastic anemia, and agranulocytosis. Monitor blood counts at the beginning of each 28-day cycle of therapy, and every 2 weeks while on therapy with albendazole in all patients. Patients with liver disease and patients with hepatic echinococcosis are at increased risk for bone marrow suppression and warrant more frequent monitoring of blood counts. Discontinue albendazole if clinically significant decreases in blood cell counts occur.

5.2 Embryo-fetal Toxicity

Albendazole may cause fetal harm and should not be used in pregnant women except in clinical circumstances where no alternative management is appropriate. Obtain pregnancy test prior to prescribing albendazole to women of reproductive potential. Advise women of reproductive potential to use effective birth control for the duration of albendazole therapy and for one month after end of therapy. Immediately discontinue albendazole if a patient becomes pregnant and apprise the patient of the potential hazard to the fetus [see Use in Specific Populations (8.1, 8.3)].

5.3 Risk of Neurologic Symptoms in Neurocysticercosis

Patients being treated for neurocysticercosis should receive steroid and anticonvulsant therapy to prevent neurological symptoms (e.g. seizures, increased intracranial pressure and focal signs) as a result of an inflammatory reaction caused by death of the parasite within the brain.

5.4 Risk of Retinal Damage in Patients with Retinal Neurocysticercosis

Cysticercosis may involve the retina. Before initiating therapy for neurocysticercosis, examine the patient for the presence of retinal lesions. If such lesions are visualized, weigh the need for anticysticeral therapy against the possibility of retinal damage resulting from inflammatory damage caused by albendazole-induced death of the parasite.

5.5 Hepatic Effects

In clinical trials, treatment with albendazole has been associated with mild to moderate elevations of hepatic enzymes in approximately 16% of patients. These elevations have generally returned to normal upon discontinuation of therapy. There have also been case reports of acute liver failure of uncertain causality and hepatitis [see Adverse Reactions (6)].

Monitor liver enzymes (transaminases) before the start of each treatment cycle and at least every 2 weeks during treatment. If hepatic enzymes exceed twice the upper limit of normal, consideration should be given to discontinuing albendazole therapy based on individual patient circumstances. Restarting albendazole treatment in patients whose hepatic enzymes have normalized off treatment is an individual decision that should take into account the risk/benefit of further albendazole usage. Perform laboratory tests frequently if albendazole treatment is restarted.

Patients with elevated liver enzyme test results are at increased risk for hepatotoxicity and bone marrow suppression [see Warnings and Precautions (5.1)]. Discontinue therapy if liver enzymes are significantly increased or if clinically significant decreases in blood cell counts occur.

5.6 Unmasking of Neurocysticercosis in Hydatid Patients

Undiagnosed neurocysticercosis may be uncovered in patients treated with albendazole for other conditions. Patients with epidemiologic factors who are at risk for neurocysticercosis should be evaluated prior to initiation of therapy.

6 ADVERSE REACTIONS

6.1 Clinical Trials Experience

Because clinical trials are conducted under widely varying conditions, adverse reaction rates observed in the clinical trials of a drug cannot be directly compared to rates in the clinical trials of another drug and may not reflect the rates observed in practice.

The adverse reaction profile of albendazole differs between hydatid disease and neurocysticercosis. Adverse reactions occurring with a frequency of 1% or greater in either disease are described in Table 2 below.

These symptoms were usually mild and resolved without treatment. Treatment discontinuations were predominantly due to leukopenia (0.7%) or hepatic abnormalities (3.8% in hydatid disease). The following incidence reflects adverse reactions that were reported to be at least possibly or probably related to albendazole.

Table 2: Adverse Reaction Incidence 1% or Greater in Hydatid Disease and Neurocysticercosis

Adverse Reaction | Hydatid Disease | Neurocysticercosis
Gastrointestinal
Abdominal Pain | 6 | 0
Nausea | 4 | 6
Vomiting | 4 | 6
General disorders and administration site conditions
Fever | 1 | 0
Investigations
Elevated Hepatic Enzymes | 16 | less than 1
Nervous system disorders
Dizziness | 1 | less than 1
Headache | 1 | 11
Meningeal Signs | 0 | 1
Raised Intracranial Pressure | 0 | 2
Vertigo | 1 | less than 1
Skin and subcutaneous tissue disorders
Reversible Alopecia | 2 | less than 1

The following adverse events were observed at an incidence of less than 1%:

Blood and Lymphatic System Disorders: There have been reports of leukopenia, granulocytopenia, pancytopenia, agranulocytosis, or thrombocytopenia [see Warnings and Precautions (5.1)].

Immune System Disorders: Hypersensitivity reactions, including rash and urticaria.

6.2 Postmarketing Experience

The following adverse reactions have been identified during post-approval use of albendazole. Because these reactions are reported voluntarily from a population of uncertain size, it is not always possible to reliably estimate their frequency or establish a causal relationship to drug exposure.

Blood and Lymphatic System Disorders: Aplastic anemia, bone marrow suppression, neutropenia.

Eye Disorders: Vision blurred.

Gastrointestinal Disorders: Diarrhea.

General System Disorders: Asthenia.

Hepatobiliary Disorders: Elevations of hepatic enzymes, hepatitis, acute liver failure.

Musculoskeletal and Connective Tissue Disorders: Rhabdomyolysis.

Nervous System Disorders: Somnolence, convulsion.

Renal and Urinary Disorders: Acute renal failure.

Skin and Subcutaneous Tissue Disorders: Erythema multiforme, Stevens-Johnson syndrome.

7 DRUG INTERACTIONS

7.1 Dexamethasone

Steady-state trough concentrations of albendazole sulfoxide were about 56% higher when 8 mg dexamethasone was co-administered with each dose of albendazole (15 mg/kg/day) in 8 neurocysticercosis patients.

7.2 Praziquantel

In the fed state, praziquantel (40 mg/kg) increased mean maximum plasma concentration and area under the curve of albendazole sulfoxide by about 50% in healthy subjects (n = 10) compared with a separate group of subjects (n = 6) given albendazole alone. Mean Tmax and mean plasma elimination half-life of albendazole sulfoxide were unchanged. The pharmacokinetics of praziquantel were unchanged following co-administration with albendazole (400 mg).

7.3 Cimetidine

Albendazole sulfoxide concentrations in bile and cystic fluid were increased (about 2-fold) in hydatid cyst patients treated with cimetidine (10 mg/kg/day) (n = 7) compared with albendazole (20 mg/kg/day) alone (n = 12). Albendazole sulfoxide plasma concentrations were unchanged 4 hours after dosing.

7.4 Theophylline

Following a single dose of albendazole (400 mg), the pharmacokinetics of theophylline (aminophylline 5.8 mg/kg infused over 20 minutes) were unchanged. Albendazole induces cytochrome P450 1A in human hepatoma cells; therefore, it is recommended that plasma concentrations of theophylline be monitored during and after treatment.

8 USE IN SPECIFIC POPULATIONS

8.1 Pregnancy

Risk Summary

There are limited data on use of albendazole in pregnant women to inform a drug-associated risk of major birth defects and miscarriage. In published studies, single-dose albendazole exposure during pregnancy did not show evidence of an increased risk of adverse maternal or fetal outcomes; however, this finding cannot be extrapolated to multiple-dose exposures (see Data).

In animal reproductive studies, oral administration of albendazole during gestation caused embryotoxicity and skeletal malformations in pregnant rats (at oral doses of 0.10 times and 0.32 times the recommended human dose based on body surface area in mg/m^2) and pregnant rabbits (at oral doses of 0.60 times the recommended human dose based on body surface area in mg/m^2). Albendazole was also associated with maternal toxicity in rabbits (at doses of 0.60 times the recommended human dose based on body surface area in mg/m^2) (see Data).

Albendazole should be used during pregnancy only if the potential benefit justifies the potential risk to the fetus. Albendazole should not be used in pregnant women except in clinical circumstances where no alternative management is appropriate. If a patient becomes pregnant while taking this drug, albendazole should be discontinued immediately. If pregnancy occurs while taking this drug, the patient should be apprised of the potential hazard to the fetus.

The estimated background risk of major birth defects and miscarriage for the indicated population is unknown. In the U.S. general population, the estimated background risk of major birth defects and miscarriage in clinically recognized pregnancies is 2 to 4% and 15 to 20%, respectively.

Data

Human Data

A Cochrane review could not provide sufficient evidence of the impact of antihelminthics (including albendazole) on the pregnancy outcomes of low birthweight, perinatal mortality and preterm birth. In a large trial of about 2507 women, albendazole use during the second or third trimester of pregnancy had no overall effect on birth weight, perinatal mortality, or congenital anomalies. With a limited sample size and single-does exposure, another study could not rule out a two-fold increased risk of major malformations [4.7% vs. 2.2%; OR 2.2 (95% confidence interval (CI) 0.5 to 10.1); p = 0.26].

Animal Data

Albendazole has been shown to be teratogenic (to cause embryotoxicity and skeletal malformations) in pregnant rats and rabbits. The teratogenic response in the rat was shown at oral doses of 10 and 30 mg/kg/day (0.10 times and 0.32 times the recommended human dose based on body surface area in mg/m^2, respectively) during gestation days 6 to 15 and in pregnant rabbits at oral doses of 30 mg/kg/day (0.60 times the recommended human dose based on body surface area in mg/m^2) administered during gestation days 7 to 19. In the rabbit study, maternal toxicity (33% mortality) was noted at 30 mg/kg/day. In mice, no teratogenic effects were observed at oral doses up to 30 mg/kg/day (0.16 times the recommended human dose based on body surface area in mg/m^2), administered during gestation days 6 to 15.

8.2 Lactation

Risk Summary

There are no data on the presence of albendazole in human milk, the effects on the breast-fed infant or the effects on milk production. Albendazole is excreted in animal milk.

The developmental and health benefits of breastfeeding should be considered along with the mother’s clinical need for albendazole and any potential adverse effects on the breastfed child from albendazole or from the underlying maternal condition.

8.3 Females and Males of Reproductive Potential

Pregnancy Testing

Obtain pregnancy test prior to prescribing albendazole to women of reproductive potential.

Contraception

Females

Advise women of reproductive potential to use effective birth control for the duration of albendazole therapy and for one month after end of therapy.

8.4 Pediatric Use

Hydatid disease is uncommon in infants and young children. In neurocysticercosis, the efficacy of albendazole in children appears to be similar to that in adults.

8.5 Geriatric Use

In patients aged 65 and older with either hydatid disease or neurocysticercosis, there was insufficient data to determine whether the safety and effectiveness of albendazole is different from that of younger patients.

8.6 Patients with Impaired Renal Function

The pharmacokinetics of albendazole in patients with impaired renal function has not been studied.

8.7 Patients with Extra-Hepatic Obstruction

In patients with evidence of extrahepatic obstruction (n = 5), the systemic availability of albendazole sulfoxide was increased, as indicated by a 2-fold increase in maximum serum concentration and a 7-fold increase in area under the curve. The rate of absorption/conversion and elimination of albendazole sulfoxide appeared to be prolonged with mean Tmax and serum elimination half-life values of 10 hours and 31.7 hours, respectively. Plasma concentrations of parent albendazole were measurable in only 1 of 5 patients.

10 OVERDOSAGE

In case of overdosage, symptomatic therapy and general supportive measures are recommended.

11 DESCRIPTION

Albendazole is an orally administered anthelmintic drug. Chemically, it is methyl 5-(propylthio)-2-benzimidazolecarbamate. Its molecular formula is C12H15N3O2S. Its molecular weight is 265.34. It has the following chemical structure:

Albendazole is a white to yellowish powder. It is freely soluble in anhydrous formic acid and very slightly soluble in ether and in methylene chloride. Albendazole is practically insoluble in alcohol and in water.

Each white to off-white, circular, biconvex, bevel-edged film coated, TILTAB tablet is debossed with “ap” and “550” and contains 200 mg of albendazole.

Inactive ingredients consist of: carnauba wax, hypromellose, lactose monohydrate, magnesium stearate, microcrystalline cellulose, povidone, sodium lauryl sulfate, sodium saccharin, sodium starch glycolate, and starch.

12 CLINICAL PHARMACOLOGY

12.1 Mechanism of Action

Albendazole is a synthetic, antihelminthic drug of the class benzimidazole [see Clinical Pharmacology (12.4)].

12.3 Pharmacokinetics

Absorption

Albendazole is poorly absorbed from the gastrointestinal tract due to its low aqueous solubility. Albendazole concentrations are negligible or undetectable in plasma as it is rapidly converted to the sulfoxide metabolite prior to reaching the systemic circulation. The systemic anthelmintic activity has been attributed to the primary metabolite, albendazole sulfoxide. Oral bioavailability appears to be enhanced when albendazole is coadministered with a fatty meal (estimated fat content 40 grams) as evidenced by higher (up to 5-fold on average) plasma concentrations of albendazole sulfoxide as compared to the fasted state.

Maximal plasma concentrations of albendazole sulfoxide were achieved 2 hours to 5 hours after dosing and were on average 1310 ng/mL (range 460 ng/mL to 1580 ng/mL) following oral doses of albendazole (400 mg) in 6 hydatid disease patients, when administered with a fatty meal. Plasma concentrations of albendazole sulfoxide increased in a dose-proportional manner over the therapeutic dose range following ingestion of a high-fat meal (fat content 43.1 grams). The mean apparent terminal elimination half-life of albendazole sulfoxide ranged from 8 hours to 12 hours in 25 healthy subjects, as well as in 14 hydatid and 8 neurocysticercosis patients.

Following 4 weeks of treatment with albendazole (200 mg three times daily), 12 patients’ plasma concentrations of albendazole sulfoxide were approximately 20% lower than those observed during the first half of the treatment period, suggesting that albendazole may induce its own metabolism.

Distribution

Albendazole sulfoxide is 70% bound to plasma protein and is widely distributed throughout the body; it has been detected in urine, bile, liver, cyst wall, cyst fluid, and cerebrospinal fluid (CSF). Concentrations in plasma were 3-fold to 10-fold and 2-fold to 4-fold higher than those simultaneously determined in cyst fluid and CSF, respectively.

Metabolism and Excretion

Albendazole is rapidly converted in the liver to the primary metabolite, albendazole sulfoxide, which is further metabolized to albendazole sulfone and other primary oxidative metabolites that have been identified in human urine. Following oral administration, albendazole has not been detected in human urine. Urinary excretion of albendazole sulfoxide is a minor elimination pathway with less than 1% of the dose recovered in the urine. Biliary elimination presumably accounts for a portion of the elimination as evidenced by biliary concentrations of albendazole sulfoxide similar to those achieved in plasma.

Specific Populations

Pediatrics

Following single-dose administration of 200 mg to 300 mg (approximately 10 mg/kg) albendazole to 3 fasted and 2 fed pediatric patients with hydatid cyst disease (age range 6 to 13 years), albendazole sulfoxide pharmacokinetics were similar to those observed in fed adults.

Geriatrics

Although no studies have investigated the effect of age on albendazole sulfoxide pharmacokinetics, data in 26 hydatid cyst patients (up to 79 years) suggest pharmacokinetics similar to those in young healthy subjects.

12.4 Microbiology

Mechanism of Action

Albendazole binds to the colchicine-sensitive site of β-tubulin inhibiting their polymerization into microtubules. The decrease in microtubules in the intestinal cells of the parasites decreases their absorptive function, especially the uptake of glucose by the adult and larval forms of the parasites, and also depletes glycogen storage. Insufficient glucose results in insufficient energy for the production of adenosine trisphosphate (ATP) and the parasite eventually dies.

Mechanism of Resistance

Parasitic resistance to albendazole is caused by changes in amino acids that result in changes in the β-tubulin protein. This causes reduced binding of the drug to β-tubulin.

In the specified treatment indications albendazole appears to be active against the larval forms of the following organisms:

Echinococcus granulosus

Taenia solium

13 NONCLINICAL TOXICOLOGY

13.1 Carcinogenesis, Mutagenesis, Impairment of Fertility

Long-term carcinogenicity studies were conducted in mice and rats.

No evidence of increased incidence of tumors was found in the mice or rats at up to 400 mg/kg/day or 20 mg/kg/day respectively (2 times and 0.2 times the recommended human dose on a body surface area basis).

In genotoxicity tests, albendazole was found negative in an Ames Salmonella/Microsome Plate mutation assay, Chinese Hamster Ovary chromosomal aberration test, and in vivo mouse micronucleus test. In the in vitro BALB/3T3 cells transformation assay, albendazole produced weak activity in the presence of metabolic activation while no activity was found in the absence of metabolic activation.

Albendazole did not adversely affect male or female fertility in the rat at an oral dose of 30 mg/kg/day (0.32 times the recommended human dose based on body surface area in mg/m^2).

16 HOW SUPPLIED/STORAGE AND HANDLING

16.1 How Supplied

Each white to off-white, circular, biconvex, bevel-edged film coated, TILTAB tablet is debossed with “ap” and “550” and contains 200 mg of albendazole.

Bottles of 2 Tablets NDC 0115-1701-49

16.2 Storage and Handling

Store at 20° to 25°C (68° to 77°F) [See USP Controlled Room Temperature].

17 PATIENT COUNSELING INFORMATION

Patients should be advised that:

- Some people, particularly children, may experience difficulties swallowing the albendazole tablets whole.
- Take albendazole with food.
- Albendazole may cause fetal harm, therefore, obtain a pregnancy test in women of reproductive potential prior to initiating therapy [see Use in Specific Populations (8.1, 8.3)].
- Advise women of reproductive potential to use effective birth control while on albendazole and for one month after completing treatment [see Use in Specific Populations (8.3)].
- During albendazole therapy, monitor blood counts and liver enzymes every 2 weeks because of the possibility of harm to the liver or bone marrow [see Warnings and Precautions (5.5)].

TILTAB is a registered trademark of GlaxoSmithKline, used with permission.

Manufactured by:
GlaxoSmithKline
Mississauga, Ontario
L5N 6L4 Canada

Distributed by:
Amneal Pharmaceuticals LLC
Bridgewater, NJ 08807

1905-03

Rev. 09-2019-01